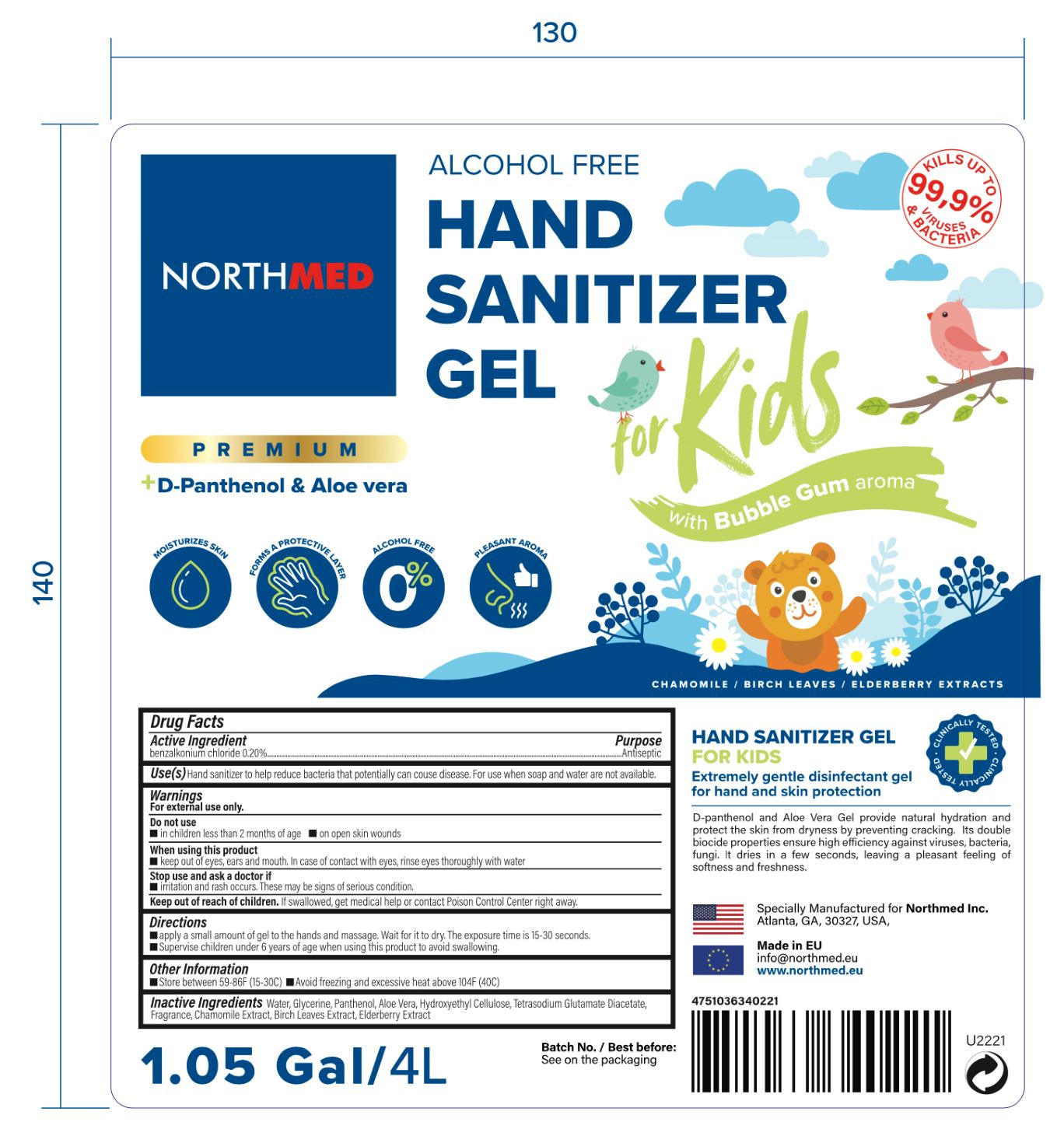 DRUG LABEL: Hand Sanitizer
NDC: 78522-103 | Form: GEL
Manufacturer: Northmed
Category: otc | Type: HUMAN OTC DRUG LABEL
Date: 20210324

ACTIVE INGREDIENTS: BENZALKONIUM CHLORIDE 2 mg/4 L
INACTIVE INGREDIENTS: GLYCERIN; FRAGRANCE FLORAL ORC0902236; WATER; CHAMOMILE FLOWER OIL; HYDROXYETHYL CELLULOSE, UNSPECIFIED; PANTHENOL; TETRASODIUM GLUTAMATE DIACETATE; ALOE VERA LEAF; BIRCH TRITERPENES

Active Ingredient

Benzalkonium Chloride, .2%. Purpose: Antiseptic

Purpose

Antiseptic

Use

Hand Sanitizer to help reduce bacteria that potentially can cause disease. For use when soap and water are not available.

Warnings

For external use only.

Do not use

- in children less than 2 months of age
- on open skin wounds

When using this product keep out of eyes, ears, and mouth. In case of contact with eyes, rinse eyes thoroughly with water.
Stop use and ask a doctor if irritation or rash occurs. These may be signs of a serious condition.
Keep out of reach of children. If swallowed, get medical help or contact a Poison Control Center right away.

Stop use and ask a doctor if irritation or rash occurs. These may be signs of a serious condition.

Keep out of reach of children. If swallowed, get medical help or contact a Poison Control Center right away.

Directions

Apply a small amount of gel to the hands and massage. Wait for it to dry. The exposure time is 15-30 seconds. Supervise children under 6 years of age when using this product to avoid swallowing.

Other information

- Store between 41-80F (5-27C).
- Avoid freezing and excessive heat above 104F (40C).

Inactive ingredients

Water. glycerin, panthenol, aloe vera, hydroxyethyl cellulose, tetrasodium glutamate diacetate, fragrance, chamomile extract, birch leaf extract, elderberry extract

Package Label - Principal Display Panel

4L NDC: 78522-101-01